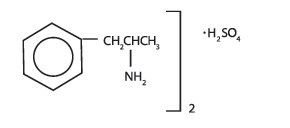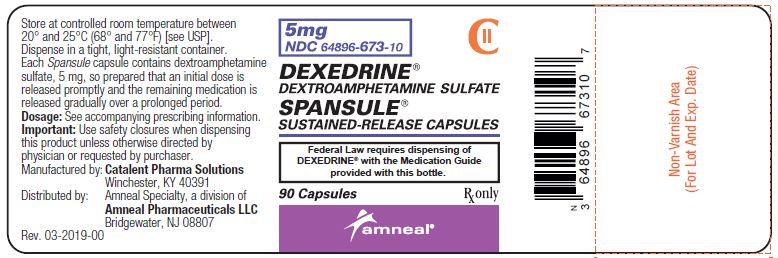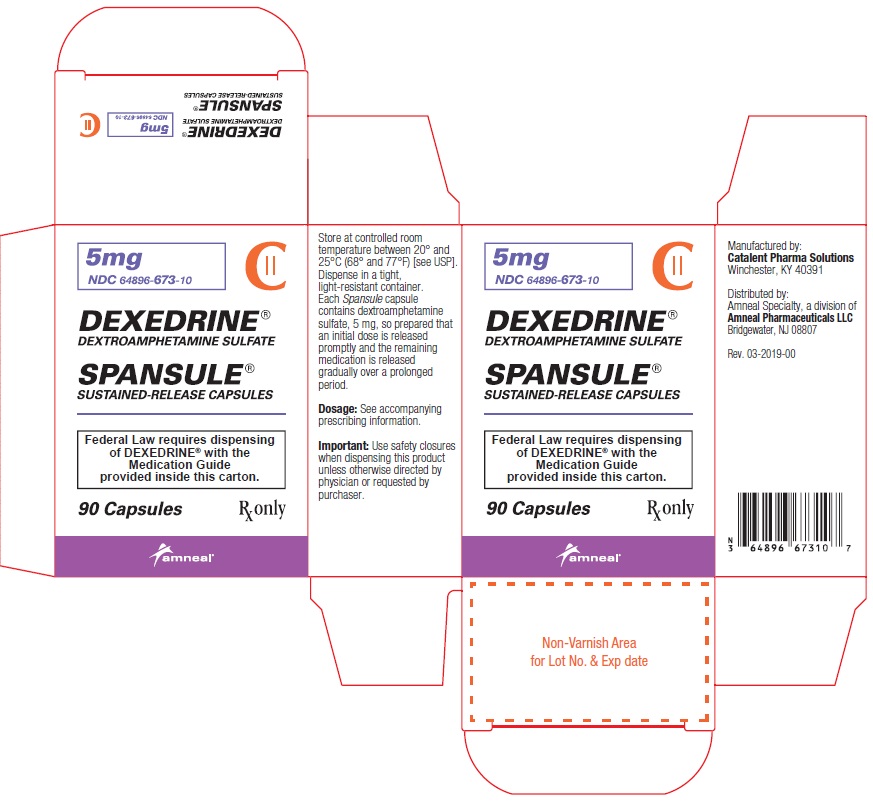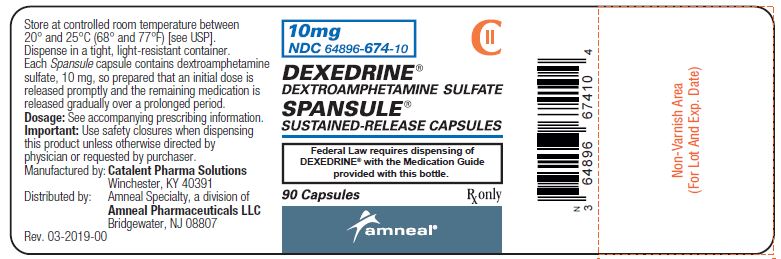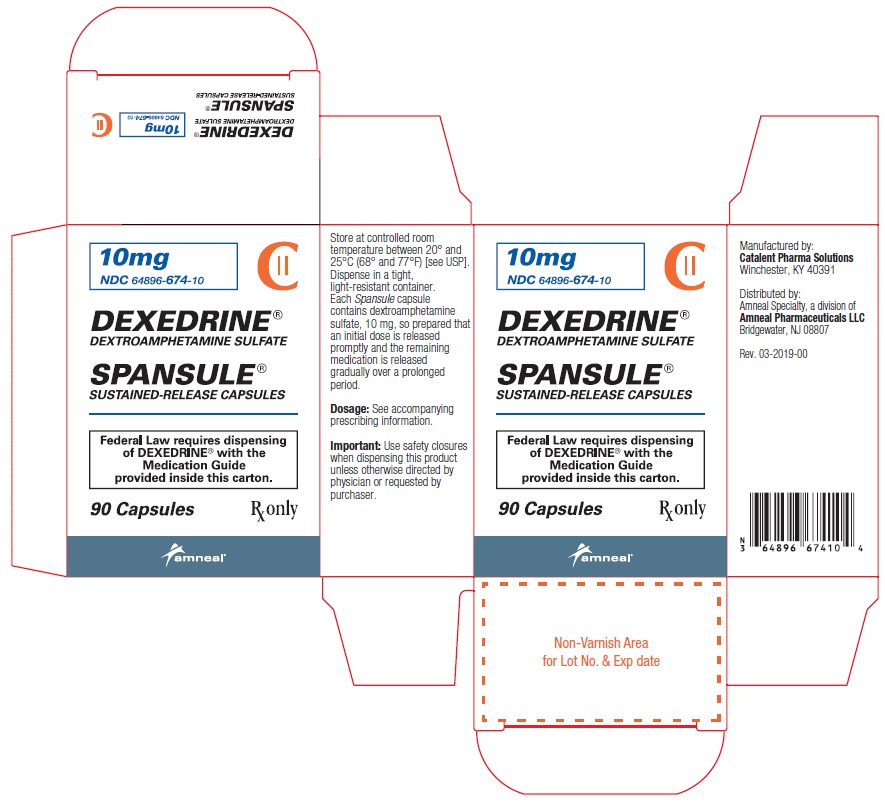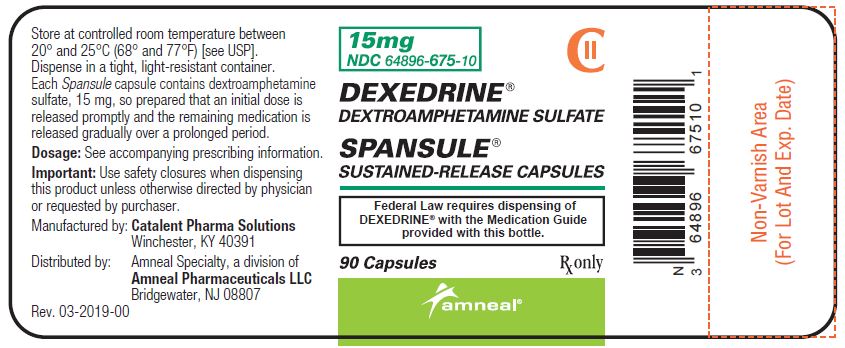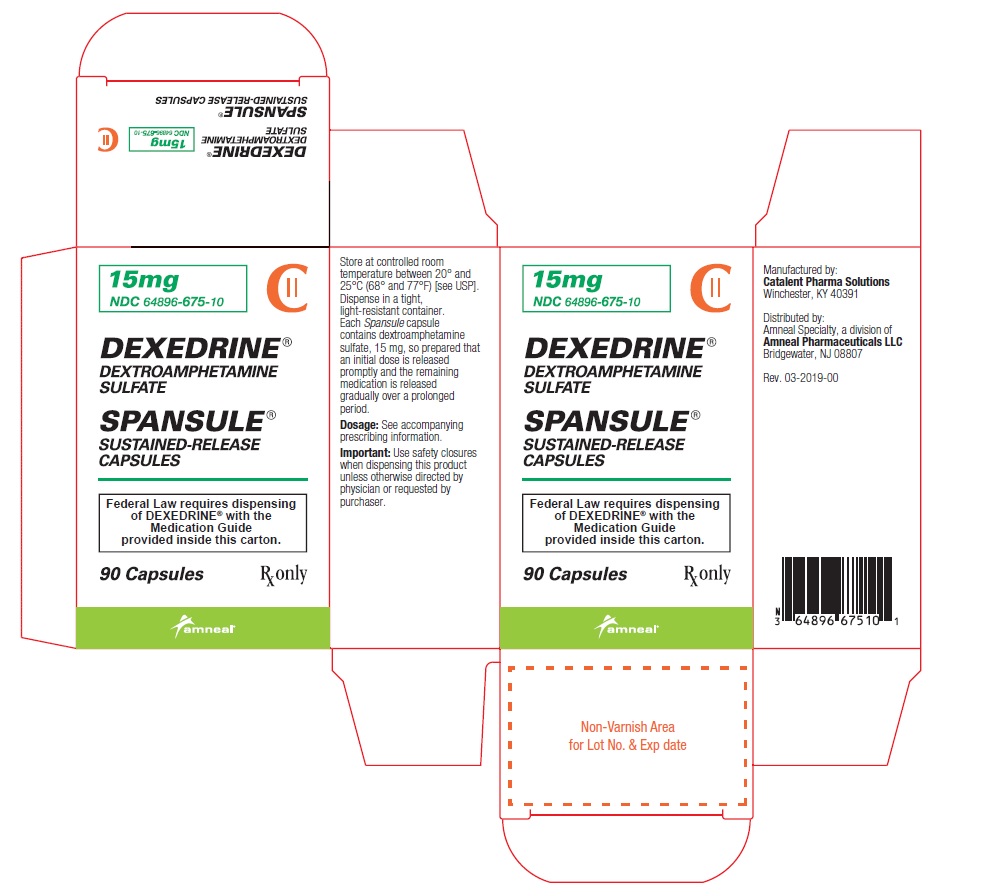 DRUG LABEL: DEXEDRINE
NDC: 64896-673 | Form: CAPSULE, EXTENDED RELEASE
Manufacturer: Amneal Pharmaceuticals LLC
Category: prescription | Type: HUMAN PRESCRIPTION DRUG LABEL
Date: 20250925
DEA Schedule: CII

ACTIVE INGREDIENTS: DEXTROAMPHETAMINE SULFATE 5 mg/1 1
INACTIVE INGREDIENTS: CETYL ALCOHOL; D&C YELLOW NO. 10; DIBUTYL SEBACATE; ETHYLCELLULOSES; FD&C BLUE NO. 1; FD&C RED NO. 40; FD&C YELLOW NO. 6; GELATIN; HYPROMELLOSES; POLYETHYLENE GLYCOL, UNSPECIFIED; POVIDONE; SODIUM LAURYL SULFATE

DEXEDRINE®
(dextroamphetamine sulfate) SPANSULE® sustained-release capsules, CII
Rx Only

WARNING: ABUSE, MISUSE, AND ADDICTION

DEXEDRINE has a high potential for abuse and misuse, which can lead to the development of a substance use disorder, including addiction. Misuse and abuse of CNS stimulants, including DEXEDRINE, can result in overdose and death [see Overdosage], and this risk is increased with higher doses or unapproved methods of administration, such as snorting or injection.

Before prescribing DEXEDRINE, assess each patient’s risk for abuse, misuse, and addiction. Educate patients and their families about these risks, proper storage of the drug, and proper disposal of any unused drug. Throughout DEXEDRINE treatment, reassess each patient’s risk of abuse, misuse, and addiction and frequently monitor for signs and symptoms of abuse, misuse, and addiction [see Warnings and Drug Abuse and Dependence].

DESCRIPTION

DEXEDRINE (dextroamphetamine sulfate) is the dextro isomer of the compound d,l-amphetamine sulfate, a sympathomimetic amine of the amphetamine group. Chemically, dextroamphetamine is d-alpha-methylphenethylamine, and is present in all forms of DEXEDRINE as the neutral sulfate.

Structural formula:

SPANSULE capsules

Each SPANSULE sustained-release capsule is so prepared that an initial dose is released promptly and the remaining medication is released gradually over a prolonged period.

Each capsule, with brown cap and natural body, contains dextroamphetamine sulfate. The 5-mg capsule is imprinted in white with IX and 5 mg on the brown cap and is imprinted in white with 673 and 5 mg on the natural body. The 10-mg capsule is imprinted in white with IX and 10 mg on the brown cap and is imprinted in white with 674 and 10 mg on the natural body. The 15-mg capsule is imprinted in white with IX and 15 mg on the brown cap and is imprinted in white with 675 and 15 mg on the natural body. Product reformulation in 1996 has caused a minor change in the color of the time-released pellets within each capsule. Inactive ingredients now consist of cetyl alcohol, D&C Yellow No. 10, dibutyl sebacate, ethylcellulose, FD&C Blue No. 1, FD&C Red No. 40, FD&C Yellow No. 6, gelatin, hypromellose, polyethylene glycol, povidone, sodium lauryl sulfate, sugar spheres, and trace amounts of other inactive ingredients.

CLINICAL PHARMACOLOGY

Amphetamines are noncatecholamine, sympathomimetic amines with CNS stimulant activity. Peripheral actions include elevations of systolic and diastolic blood pressures and weak bronchodilator and respiratory stimulant action. There is neither specific evidence that clearly establishes the mechanism whereby amphetamines produce mental and behavioral effects in children, nor conclusive evidence regarding how these effects relate to the condition of the central nervous system. DEXEDRINE SPANSULE Capsules are formulated to release the active drug substance in vivo in a more gradual fashion than the standard formulation, as demonstrated by blood levels. The formulation has not been shown superior in effectiveness over the same dosage of the standard, noncontrolled-release formulations given in divided doses.

Pharmacokinetics

The pharmacokinetics of the tablet and sustained-release capsule were compared in 12 healthy subjects. The extent of bioavailability of the sustained-release capsule was similar compared to the immediate-release tablet. Following administration of three 5-mg tablets, average maximal dextroamphetamine plasma concentrations (Cmax) of 36.6 ng/mL were achieved at approximately 3 hours.

Following administration of one 15-mg sustained-release capsule, maximal dextroamphetamine plasma concentrations were obtained approximately 8 hours after dosing. The average Cmax was 23.5 ng/mL. The average plasma T&frac12; was similar for both the tablet and sustained-release capsule and was approximately 12 hours. In 12 healthy subjects, the rate and extent of dextroamphetamine absorption were similar following administration of the sustained-release capsule formulation in the fed (58 g to 75 g fat) and fasted state.

INDICATIONS AND USAGE

DEXEDRINE is indicated in:

Narcolepsy

Attention Deficit Disorder with Hyperactivity

As an integral part of a total treatment program that typically includes other measures (psychological, educational, social) for patients (ages 6 years to 16 years) with this syndrome. A diagnosis of Attention Deficit Hyperactivity Disorder (ADHD; DSM-IV) implies the presence of the hyperactive-impulsive or inattentive symptoms that caused impairment and were present before age 7 years. The symptoms must cause clinically significant impairment, e.g., in social, academic, or occupational functioning, and be present in 2 or more settings, e.g., school (or work) and at home. The symptoms must not be better accounted for by another mental disorder. For the Inattentive Type, at least 6 of the following symptoms must have persisted for at least 6 months: lack of attention to details/careless mistakes; lack of sustained attention; poor listener; failure to follow through on tasks; poor organization; avoids tasks requiring sustained mental effort; loses things; easily distracted; forgetful. For the Hyperactive-Impulsive Type, at least 6 of the following symptoms must have persisted for at least 6 months: fidgeting/squirming; leaving seat; inappropriate running/climbing; difficulty with quiet activities; “on the go”; excessive talking; blurting answers; can't wait turn; intrusive. The Combined Type requires both inattentive and hyperactive-impulsive criteria to be met.

Special Diagnostic Considerations

Specific etiology of this syndrome is unknown, and there is no single diagnostic test. Adequate diagnosis requires the use of medical and special psychological, educational, and social resources. Learning may or may not be impaired. The diagnosis must be based upon a complete history and evaluation of the patient and not solely on the presences of the required number of DSM-IV characteristics.

Need for Comprehensive Treatment Program

DEXEDRINE is indicated as an integral part of a total treatment program for ADHD that may include other measures (psychological, educational, social) for patients with this syndrome. Drug treatment may not be indicated for all patients with this syndrome. Stimulants are not intended for use in patients who exhibit symptoms secondary to environmental factors and/or other primary psychiatric disorders, including psychosis. Appropriate educational placement is essential and psychosocial intervention is often helpful. When remedial measures alone are insufficient, the decision to prescribe stimulant medication will depend upon the physician’s assessment of the chronicity and severity of the patient’s symptoms.

Limitations of Use

The use of DEXEDRINE is not recommended in pediatric patients younger than 6 years of age because they had higher plasma exposure and a higher incidence of adverse reactions (e.g., weight loss) than patients 6 years and older at the same dosage [see Precautions, Pediatric Use].

CONTRAINDICATIONS

In patients known to be hypersensitive to amphetamine, or other components of DEXEDRINE. Hypersensitivity reactions such as angioedema and anaphylactic reactions have been reported in patients treated with other amphetamine products [see Adverse Reactions].

Patients taking monoamine oxidase inhibitors (MAOIs), or within 14 days of stopping MAOIs (including MAOIs such as linezolid or intravenous methylene blue), because of an increased risk of hypertensive crisis [see Warnings and Drug Interactions].

WARNINGS

Abuse, Misuse, and Addiction

DEXEDRINE has a high potential for abuse and misuse. The use of DEXEDRINE exposes individuals to the risks of abuse and misuse, which can lead to the development of a substance use disorder, including addiction. DEXEDRINE can be diverted for non-medical use into illicit channels or distribution [see Drug Abuse and Dependence]. Misuse and abuse of CNS stimulants, including DEXEDRINE can result in overdose and death [see Overdosage], and this risk is increased with higher doses or unapproved methods of administration, such as snorting or injection.

Before prescribing DEXEDRINE, assess each patient’s risk for abuse, misuse, and addiction. Educate patients and their families about these risks and proper disposal of any unused drug. Advise patients to store amphetamine sulfate in a safe place, preferably locked, and instruct patients to not give DEXEDRINE to anyone else. Throughout DEXEDRINE treatment, reassess each patient’s risk of abuse, misuse, and addiction and frequently monitor for signs and symptoms of abuse, misuse, and addiction.

Risks to Patients with Serious Cardiac Disease

Sudden death has been reported in patients with structural cardiac abnormalities or other serious cardiac disease who are treated with CNS stimulants at the recommended ADHD dosages.

Avoid DEXEDRINE use in patients with known structural cardiac abnormalities, cardiomyopathy, serious cardiac arrhythmia, coronary artery disease, or other serious cardiac disease.

Increased Blood Pressure and Heart Rate

CNS stimulants cause an increase in blood pressure (mean increase about 2 to 4 mm Hg) and heart rate (mean increase about 3 to 6 bpm).

Monitor all patients for potential tachycardia and hypertension.

Psychiatric Adverse Reactions

Exacerbation of Pre-Existing Psychosis

CNS stimulants may exacerbate symptoms of behavior disturbance and thought disorder in patients with a pre-existing psychotic disorder.

Induction of a Manic Episode in Patients with Bipolar Disease

CNS stimulants may induce a manic or mixed episode in patients. Prior to initiating treatment, screen patients for risk factors for developing a manic episode (e.g., comorbid or history of depressive symptoms or a family history of suicide, bipolar disorder, or depression).

New Psychotic or Manic Symptoms

CNS stimulants, at recommended doses, may cause psychotic or manic symptoms (e.g., hallucinations, delusional thinking, or mania) in patients without a prior history of psychotic illness or mania. In a pooled analysis of multiple short-term, placebo-controlled studies of CNS stimulants, psychotic or manic symptoms occurred in approximately 0.1% of CNS stimulant-treated patients, compared with 0% of placebo-treated patients. If such symptoms occur, consideration discontinuing DEXEDRINE.

Long-Term Suppression of Growth in Pediatric Patients

DEXEDRINE is not approved for use and is not recommended in pediatric patients below 6 years of age [see Precautions, Pediatric Use].

CNS stimulants have been associated with weight loss and slowing of growth rate in pediatric patients, including DEXEDRINE. Closely monitor growth (weight and height) in DEXEDRINE-treated pediatric patients treated with CNS stimulants.

Pediatric patients who are not growing or gaining height or weight as expected may need to have their treatment interrupted [see Precautions, Pediatric Use].

Seizures

There is some clinical evidence that stimulants may lower the convulsive threshold in patients with prior history of seizures, in patients with prior EEG abnormalities in absence of seizures, and, very rarely, in patients without a history of seizures and no prior EEG evidence of seizures. In the presence of seizures, the drug should be discontinued.

Peripheral Vasculopathy, including Raynaud’s phenomenon

Stimulants, including DEXEDRINE, used to treat ADHD are associated with peripheral vasculopathy, including Raynaud’s phenomenon. Signs and symptoms are usually intermittent and mild; however, sequelae have included digital ulceration and/or soft tissue breakdown. Effects of peripheral vasculopathy, including Raynaud’s phenomenon, were observed in post-marketing reports and at therapeutic dosages in all age groups throughout the course of treatment. Signs and symptoms generally improve after dosage reduction or discontinuation of the CNS stimulant. Careful observation for digital changes is necessary during DEXEDRINE treatment. Further clinical evaluation (e.g., rheumatology referral) may be appropriate for DEXEDRINE-treated patients who develop signs or symptoms of peripheral vasculopathy.

Serotonin Syndrome

Serotonin syndrome, a potentially life-threatening reaction, may occur when amphetamines are used in combination with other drugs that affect the serotonergic neurotransmitter systems such as monoamine oxidase inhibitors (MAOIs), selective serotonin reuptake inhibitors (SSRIs), serotonin norepinephrine reuptake inhibitors (SNRIs), triptans, tricyclic antidepressants, fentanyl, lithium, tramadol, tryptophan, buspirone, and St. John’s Wort [see Drug Interactions]. Amphetamines and amphetamine derivatives are known to be metabolized, to some degree, by cytochrome P450 2D6 (CYP2D6) and display minor inhibition of CYP2D6 metabolism [see Clinical Pharmacology]. The potential for a pharmacokinetic interaction exists with the co-administration of CYP2D6 inhibitors which may increase the risk with increased exposure to DEXEDRINE. In these situations, consider an alternative non-serotonergic drug or an alternative drug that does not inhibit CYP2D6 [see Drug Interactions].

Serotonin syndrome symptoms may include mental status changes (e.g., agitation, hallucinations, delirium, and coma), autonomic instability (e.g., tachycardia, labile blood pressure, dizziness, diaphoresis, flushing, hyperthermia), neuromuscular symptoms (e.g., tremor, rigidity, myoclonus, hyperreflexia, incoordination), seizures, and/or gastrointestinal symptoms (e.g., nausea, vomiting, diarrhea).

Concomitant use of DEXEDRINE with MAOI drugs is contraindicated [see Contraindications].

Discontinue treatment with DEXEDRINE and any concomitant serotonergic agents immediately if the above symptoms occur, and initiate supportive symptomatic treatment. If concomitant use of DEXEDRINE with other serotonergic drugs or CYP2D6 inhibitors is clinically warranted, initiate DEXEDRINE with lower doses, monitor patients for the emergence of serotonin syndrome during drug initiation or titration, and inform patients of the increased risk for serotonin syndrome.

Motor and Verbal Tics, and Worsening of Tourette’s Syndrome

CNS stimulants, including amphetamine sulfate, have been associated with the onset or exacerbation of motor and verbal tics. Worsening of Tourette’s syndrome has also been reported. Before initiating DEXEDRINE, assess the family history and clinically evaluate patients for tics or Tourette’s syndrome. Regularly monitor patients for the emergence or worsening of tics or Tourette’s syndrome with DEXEDRINE, and discontinue treatment if clinically appropriate.

PRECAUTIONS

General

The least amount feasible should be prescribed or dispensed at 1 time in order to minimize the possibility of overdosage.

Information for Patients

Advise the patient to read the FDA-approved patient labeling (Medication Guide).

Abuse, Misuse, and Addiction

Educate patients and their families about the risks of abuse, misuse, and addiction of DEXEDRINE, which can lead to overdose and death, and proper disposal of any unused drug [see Warnings, Drug Abuse and Dependence, Overdosage]. Advise patients to store DEXEDRINE in a safe place, preferably locked, and instruct patients to not give DEXEDRINE to anyone else.

Risks to Patients with Serious Cardiac Disease

Advise patients that there are potential risks to patients with serious cardiac disease, including sudden death, with DEXEDRINE use. Instruct patients to contact a healthcare provider immediately if they develop symptoms such as exertional chest pain, unexplained syncope, or other symptoms suggestive of cardiac disease [see Warnings].

Increased Blood Pressure and Heart Rate

Instruct patients that DEXEDRINE can elevate blood pressure and heart rate [see Warnings].

Psychiatric Adverse Reactions

Advise patients that DEXEDRINE, at recommended doses, can cause psychotic or manic symptoms, even in patients without prior history of psychotic symptoms or mania [see Warnings].

Long-Term Suppression of Growth in Pediatric Patients

Advise patients that DEXEDRINE may cause slowing of growth and weight loss in pediatric patients [see Warnings].

Circulation problems in fingers and toes [Peripheral vasculopathy, including Raynaud’s phenomenon]

- Instruct patients beginning treatment with DEXEDRINE about the risk of peripheral vasculopathy, including Raynaud’s phenomenon, and associated signs and symptoms: fingers or toes may feel numb, cool, painful, and/or may change color from pale, to blue, to red.
- Instruct patients to report to their physician any new numbness, pain, skin color change, or sensitivity to temperature in fingers or toes.
- Instruct patients to call their physician immediately with any signs of unexplained wounds appearing on fingers or toes while taking DEXEDRINE.
- Further clinical evaluation (e.g., rheumatology referral) may be appropriate for certain patients [see Warnings].

Motor and Verbal Tics, and Worsening of Tourette’s Syndrome

Advise patients that motor and verbal tics and worsening of Tourette’s Syndrome may occur during treatment with DEXEDRINE. Instruct the patients to notify their healthcare provider if emergence or worsening of tics or Tourette’s syndrome occurs [see Warnings].

Drug Interactions

Acidifying Agents

Lower blood levels and efficacy of amphetamines. Increase dose based on clinical response. Examples of acidifying agents include gastrointestinal acidifying agents (e.g., guanethidine, reserpine, glutamic acid HCl, ascorbic acid) and urinary acidifying agents (e.g., ammonium chloride, sodium acid phosphate, methenamine salts).

Adrenergic Blockers

Adrenergic blockers are inhibited by amphetamines.

Alkalinizing Agents

Increase blood levels and potentiate the action of amphetamine. Co-administration of DEXEDRINE and gastrointestinal alkalinizing agents should be avoided. Examples of alkalinizing agents include gastrointestinal alkalinizing agents (e.g., sodium bicarbonate) and urinary alkalinizing agents (e.g. acetazolamide, some thiazides).

Tricyclic Antidepressants

May enhance the activity of tricyclic or sympathomimetic agents causing striking and sustained increases in the concentration of d-amphetamine in the brain; cardiovascular effects can be potentiated. Monitor frequently and adjust or use alternative therapy based on clinical response. Examples of tricyclic antidepressants include desipramine, Protriptyline.

CYP2D6 Inhibitors

The concomitant use of DEXEDRINE and CYP2D6 inhibitors may increase the exposure of DEXEDRINE compared to the use of the drug alone and increase the risk of serotonin syndrome. Initiate with lower doses and monitor patients for signs and symptoms of serotonin syndrome particularly during DEXEDRINE initiation and after a dosage increase. If serotonin syndrome occurs, discontinue DEXEDRINE and the CYP2D6 inhibitor [see Warnings, Overdosage]. Examples of CYP2D6 Inhibitors include paroxetine and fluoxetine (also serotonergic drugs), quinidine, ritonavir.

Serotonergic Drugs

The concomitant use of DEXEDRINE and serotonergic drugs increases the risk of serotonin syndrome. Initiate with lower doses and monitor patients for signs and symptoms of serotonin syndrome, particularly during DEXEDRINE initiation or dosage increase. If serotonin syndrome occurs, discontinue DEXEDRINE and the concomitant serotonergic drug(s) [see Warnings and Precautions]. Examples of serotonergic drugs include selective serotonin reuptake inhibitors (SSRI), serotonin norepinephrine reuptake inhibitors (SNRI), triptans, tricyclic antidepressants, fentanyl, lithium, tramadol, tryptophan, buspirone, St. John’s Wort.

MAO Inhibitors

Concomitant use of MAOIs and CNS stimulants can cause hypertensive crisis. Potential outcomes include death, stroke, myocardial infarction, aortic dissection, ophthalmological complications, eclampsia, pulmonary edema, and renal failure. Do not administer DEXEDRINE concomitantly or within 14 days after discontinuing MAOI [see Contraindications and Warnings]. Examples of MAOIs include selegiline, tranylcypromine, isocarboxazid, phenelzine, linezolid, methylene blue.

Proton Pump Inhibitors

Time to maximum concentration (Tmax) of amphetamine is decreased compared to when administered alone. Monitor patients for changes in clinical effect and adjust therapy based on clinical response. An example of a proton pump inhibitor is omeprazole.

Antihistamines

Amphetamines may counteract the sedative effect of antihistamines.

Antihypertensives

Amphetamines may antagonize the hypotensive effects of antihypertensives.

Chlorpromazine

Chlorpromazine blocks dopamine and norepinephrine reuptake, thus inhibiting the central stimulant effects of amphetamines, and can be used to treat amphetamine poisoning.

Ethosuximide

Amphetamines may delay intestinal absorption of ethosuximide.

Haloperidol

Haloperidol blocks dopamine and norepinephrine reuptake, thus inhibiting the central stimulant effects of amphetamines.

Lithium Carbonate

The stimulatory effects of amphetamines may be inhibited by lithium carbonate.

Meperidine

Amphetamines potentiate the analgesic effect of meperidine.

Methenamine Therapy

Urinary excretion of amphetamines is increased, and efficacy is reduced, by acidifying agents used in methenamine therapy.

Norepinephrine

Amphetamines enhance the adrenergic effect of norepinephrine.

Phenobarbital

Amphetamines may delay intestinal absorption of phenobarbital; co-administration of phenobarbital may produce a synergistic anticonvulsant action.

Phenytoin

Amphetamines may delay intestinal absorption of phenytoin; co-administration of phenytoin may produce a synergistic anticonvulsant action.

Propoxyphene

In cases of propoxyphene overdosage, amphetamine CNS stimulation is potentiated and fatal convulsions can occur.

Veratrum Alkaloids

Amphetamines inhibit the hypotensive effect of veratrum alkaloids.

Drug/Laboratory Test Interactions

Amphetamines can cause a significant elevation in plasma corticosteroid levels. This increase is greatest in the evening.

Amphetamines may interfere with urinary steroid determinations.

Carcinogenesis/Mutagenesis

Mutagenicity studies and long-term studies in animals to determine the carcinogenic potential of DEXEDRINE have not been performed.

Pregnancy

Teratogenic Effects

DEXEDRINE has been shown to have embryotoxic and teratogenic effects when administered to A/Jax mice and C57BL mice in doses approximately 41 times the maximum human dose. Embryotoxic effects were not seen in New Zealand white rabbits given the drug in doses 7 times the human dose nor in rats given 12.5 times the maximum human dose. While there are no adequate and well-controlled studies in pregnant women, there has been 1 report of severe congenital bony deformity, tracheoesophageal fistula, and anal atresia (VATER association) in a baby born to a woman who took dextroamphetamine sulfate with lovastatin during the first trimester of pregnancy. DEXEDRINE should be used during pregnancy only if the potential benefit justifies the potential risk to the fetus.

Nonteratogenic Effects

Infants born to mothers dependent on amphetamines have an increased risk of premature delivery and low birth weight. Also, these infants may experience symptoms of withdrawal as demonstrated by dysphoria, including agitation, and significant lassitude.

Nursing Mothers

Amphetamines are excreted in human milk. Mothers taking amphetamines should be advised to refrain from nursing.

Pediatric Use

The safety and effectiveness of DEXEDRINE have not been established in pediatric patients below the age of 6 years.

In studies evaluating extended-release amphetamine products, patients 4 to <6 years of age had higher systemic amphetamine exposures than those observed in older pediatric patients at the same dosage. Pediatric patients 4 to <6 years of age also had a higher incidence of adverse reactions, including weight loss.

Clinical experience suggests that in psychotic children, administration of amphetamines may exacerbate symptoms of behavior disturbance and thought disorder.

Amphetamines have been reported to exacerbate motor and phonic tics and Tourette’s syndrome. Therefore, clinical evaluation for tics and Tourette’s syndrome in children and their families should precede use of stimulant medications.

Data are inadequate to determine whether chronic administration of amphetamines may be associated with growth inhibition; therefore, growth should be monitored during treatment.

Drug treatment is not indicated in all cases of Attention Deficit Disorder with Hyperactivity and should be considered only in light of the complete history and evaluation of the child. The decision to prescribe amphetamines should depend on the physician’s assessment of the chronicity and severity of the child’s symptoms and their appropriateness for his or her age. Prescription should not depend solely on the presence of one or more of the behavioral characteristics.

When these symptoms are associated with acute stress reactions, treatment with amphetamines is usually not indicated.

ADVERSE REACTIONS

Cardiovascular

Palpitations, tachycardia, elevation of blood pressure. There have been isolated reports of cardiomyopathy associated with chronic amphetamine use.

Central Nervous System

Psychotic episodes at recommended doses (rare), overstimulation, restlessness, dizziness, insomnia, euphoria, dyskinesia, dysphoria, tremor, headache, exacerbation of motor and verbal tics, and Tourette’s syndrome.

Gastrointestinal

Dryness of the mouth, unpleasant taste, diarrhea, constipation, intestinal ischemia, and other gastrointestinal disturbances. Anorexia and weight loss may occur as undesirable effects.

Allergic

Urticaria.

Endocrine

Impotence, changes in libido, frequent or prolonged erections.

Musculoskeletal

Rhabdomyolysis.

Skin and Subcutaneous Tissue Disorders

Alopecia.

To report SUSPECTED ADVERSE REACTIONS, contact Amneal Pharmaceuticals at 1-877-835-5472 or FDA at 1-800-FDA-1088 or www.fda.gov/medwatch.

DRUG ABUSE AND DEPENDENCE

Controlled Substance

DEXEDRINE contains dextroamphetamine, a Schedule II controlled substance.

Abuse

DEXEDRINE has a high potential for abuse and misuse which can lead to the development of a substance use disorder, including addiction [see Warnings]. DEXEDRINE can be diverted for non-medical use into illicit channels or distribution.

Abuse is the intentional non-therapeutic use of a drug, even once, to achieve a desired psychological or physiological effect. Misuse is the intentional use, for therapeutic purposes, of a drug by an individual in a way other than prescribed by a health care provider or for whom it was not prescribed. Drug addiction is a cluster of behavioral, cognitive, and physiological phenomena that may include a strong desire to take the drug, difficulties in controlling drug use (e.g., continuing drug use despite harmful consequences, giving a higher priority to drug use than other activities and obligations), and possible tolerance or physical dependence.

Misuse and abuse of amphetamine may cause increased heart rate, respiratory rate, or blood pressure; sweating; dilated pupils; hyperactivity; restlessness; insomnia; decreased appetite; loss of coordination; tremors; flushed skin; vomiting; and/or abdominal pain. Anxiety, psychosis, hostility, aggression, and suicidal or homicidal ideation have also been observed with CNS stimulants abuse and/or misuse. Misuse and abuse of CNS stimulants, including DEXEDRINE, can result in overdose and death [see Overdosage], and this risk is increased with higher doses or unapproved methods of administration, such as snorting or injection.

Dependence

Physical Dependence

DEXEDRINE may produce physical dependence. Physical dependence is a state that develops as a result of physiological adaptation in response to repeated drug use, manifested by withdrawal signs and symptoms after abrupt discontinuation or a significant dose reduction of a drug.

Withdrawal signs and symptoms after abrupt discontinuation or dose reduction following prolonged use of CNS stimulants including DEXEDRINE include dysphoric mood; depression; fatigue; vivid, unpleasant dreams; insomnia or hypersomnia; increased appetite; and psychomotor retardation or agitation.

Tolerance

DEXEDRINE may produce tolerance. Tolerance is a physiological state characterized by a reduced response to a drug after repeated administration (i.e., a higher dose of a drug is required to produce the same effect that was once obtained at a lower dose).

OVERDOSAGE

Clinical Effects of Overdose

Overdose of CNS stimulants is characterized by the following sympathomimetic effects:

- Cardiovascular effects including tachyarrhythmias, and hypertension or hypotension. Vasospasm, myocardial infarction, or aortic dissection may precipitate sudden cardiac death. Takotsubo cardiomyopathy may develop.
- CNS effects including psychomotor agitation, confusion, and hallucinations. Serotonin syndrome, seizures, cerebral vascular accidents, and coma may occur.
- Life-threatening hyperthermia (temperatures greater than 104°F) and rhabdomyolysis may develop.

Overdose Management

Consider the possibility of multiple drug ingestion. The pharmacokinetic profile of DEXEDRINE should be considered when treating patients with overdose. D-amphetamine is not dialyzable. Consider contacting the Poison Help line (1-800-222-1222) or a medical toxicologist for additional overdose management recommendations.

DOSAGE AND ADMINISTRATION

Amphetamines should be administered at the lowest effective dosage and dosage should be individually adjusted. Late evening doses should be avoided because of the resulting insomnia.

Prior to treating patients with DEXEDRINE, assess:

- for the presence of cardiac disease (i.e., perform a careful history, family history of sudden death or ventricular arrhythmia, and physical exam) [see Warnings].
- the family history and clinically evaluate patients for motor or verbal tics or Tourette’s syndrome [see Warnings].

Narcolepsy

Usual dose is 5 to 60 mg per day in divided doses, depending on the individual patient response.

Narcolepsy seldom occurs in children under 12 years of age; however, when it does, DEXEDRINE may be used. The suggested initial dose for patients aged 6 to 12 is 5 mg daily; daily dose may be raised in increments of 5 mg at weekly intervals until an optimal response is obtained. In patients 12 years of age and older, start with 10 mg daily; daily dosage may be raised in increments of 10 mg at weekly intervals until an optimal response is obtained. If bothersome adverse reactions appear (e.g., insomnia or anorexia), dosage should be reduced.

SPANSULE capsules may be used for once-a-day dosage wherever appropriate.

Attention Deficit Disorder with Hyperactivity

The SPANSULE capsule formulation is not recommended for pediatric patients younger than 6 years of age.

In pediatric patients 6 years of age and older, start with 5 mg once or twice daily; daily dosage may be raised in increments of 5 mg at weekly intervals until optimal response is obtained. Only in rare cases will it be necessary to exceed a total of 40 mg per day. SPANSULE capsules may be used for once-a-day dosage wherever appropriate.

HOW SUPPLIED

DEXEDRINE SPANSULE capsules

Each capsule, with brown cap and natural body, contains dextroamphetamine sulfate.

The 5-mg capsule is imprinted in white with IX and 5 mg on the brown cap and is imprinted in white with 673 and 5 mg on the natural body.

The 10-mg capsule is imprinted in white with IX and 10 mg on the brown cap and is imprinted in white with 674 and 10 mg on the natural body.

The 15-mg capsule is imprinted in white with IX and 15 mg on the brown cap and is imprinted in white with 675 and 15 mg on the natural body.

5 mg 90s: NDC 64896-673-10

10 mg 90s: NDC 64896-674-10

15 mg 90s: NDC 64896-675-10

Store at controlled room temperature between 20° to 25°C (68° to 77°F) [see USP].

Dispense in a tight, light-resistant container.

Manufactured by:

Catalent Pharma Solutions

Winchester, KY 40391

Distributed by:

Amneal Specialty, a division of

Amneal Pharmaceuticals LLC

Bridgewater, NJ 08807

Rev. 09-2025-03

For additional copies of the printed medication guide, please visit www.amneal.com or contact us at 1-877-835-5472.

MEDICATION GUIDE

DEXEDRINE® (dek-suh-drin)

(dextroamphetamine sulfate) SPANSULE® sustained-release capsules, CII

What is the most important information I should know about DEXEDRINE?
DEXEDRINE may cause serious side effects, including:

- Abuse, misuse, and addiction. DEXEDRINE has a high chance for abuse and misuse and may lead to substance use problems, including addiction. Misuse and abuse of DEXEDRINE, other amphetamine containing medicines, and methylphenidate containing medicines, can lead to overdose and death. The risk of overdose and death is increased with higher doses of DEXEDRINE or when it is used in ways that are not approved, such as snorting or injection.
  - Your healthcare provider should check you or your child’s risk for abuse, misuse, and addiction before starting treatment with DEXEDRINE and will monitor you or your child during treatment.
  - DEXEDRINE may lead to physical dependence after prolonged use, even if taken as directed by your healthcare provider.
  - Do not give DEXEDRINE to anyone else. See “What is DEXEDRINE?” for more information.
  - Keep DEXEDRINE in a safe place and properly dispose of any unused medicine. See “How should I store DEXEDRINE?” for more information.
  - Tell your healthcare provider if you or your child have ever abused or been dependent on alcohol, prescription medicines, or street drugs.
- Risks for people with serious heart disease. Sudden death has happened in people who have heart defects or other serious heart disease.
  Your healthcare provider should check you or your child carefully for heart problems before starting DEXEDRINE. Tell your healthcare provider if you or your child have any heart problems, heart disease, or heart defects.
  Call your healthcare provider right away or go to the nearest hospital emergency room right away if you or your child have any signs of heart problems such as chest pain, shortness of breath, or fainting during treatment with DEXEDRINE.
- Increased blood pressure and heart rate.
  Your healthcare provider should check you or your child’s blood pressure and heart rate regularly during treatment with DEXEDRINE.
- Mental (psychiatric) problems, including:

- onew or worse behavior or thought problems
- onew or worse bipolar illness

- onew psychotic symptoms (such as hearing voices, or seeing or believing things that are not real) or new manic symptoms

Tell your healthcare provider about any mental problems you or your child have, or about a family history of suicide, bipolar illness, or depression.

Call your healthcare provider right away if you or your child have any new or worsening mental symptoms or problems during treatment with DEXEDRINE, especially hearing voices, seeing or believing things that are not real, or new manic symptoms.

What is DEXEDRINE?

DEXEDRINE is a central nervous system (CNS) stimulant prescription medicine used for the treatment of:

- a sleep disorder called narcolepsy.
- Attention-Deficit Hyperactivity Disorder (ADHD) in children 6 to 17 years of age.
- DEXEDRINE may help increase attention and decrease impulsiveness and hyperactivity in people with ADHD.

DEXEDRINE is not recommended for use in children under 6 years of age with ADHD.

DEXEDRINE is a federally controlled substance (CII) because it contains dextroamphetamine that can be a target for people who abuse prescription medicines or street drugs. Keep DEXEDRINE in a safe place to protect it from theft. Never give your DEXEDRINE to anyone else because it may cause death or harm them. Selling or giving away DEXEDRINE may harm others and is against the law.

Do not take DEXEDRINE if you or your child:

- are allergic to amphetamine products or any of the ingredients in DEXEDRINE. See the end of this Medication Guide for a complete list of ingredients in DEXEDRINE.
- are taking or have taken within the past 14 days, a medicine used to treat depression called a monoamine oxidase inhibitor (MAOI), including the antibiotic linezolid or the intravenous medicine methylene blue.

Before taking DEXEDRINE, tell your healthcare provider about all of your or your child’s medical conditions, including if you or your child:

- have heart problems, heart disease, heart defects, or high blood pressure
- have mental problems including psychosis, mania, bipolar illness, or depression, or have a family history of suicide, bipolar illness, or depression
- have seizures or have had an abnormal brain wave test (EEG)
- have circulation problems in fingers and toes
- have or had repeated movements or sounds (tics) or Tourette’s syndrome, or have a family history of tics or Tourette’s syndrome
- are pregnant or plan to become pregnant. It is not known if DEXEDRINE will harm the unborn baby. Tell your healthcare provider if you or your child become pregnant during treatment with DEXEDRINE.
- are breastfeeding or plan to breastfeed. DEXEDRINE passes into breast milk. You or your child should not breastfeed during treatment with DEXEDRINE. Talk to your healthcare provider about the best way to feed the baby during treatment with DEXEDRINE.

Tell your healthcare provider about all of the medicines that you or your child take, including prescription and over-the-counter medicines, vitamins, and herbal supplements.

DEXEDRINE and some medicines may interact with each other and cause serious side effects. Sometimes the doses of other medicines will need to be changed during treatment with DEXEDRINE. Your healthcare provider will decide if DEXEDRINE can be taken with other medicines.

Especially tell your healthcare provider if you or your child take:

- selective serotonin reuptake inhibitors (SSRIs)
- serotonin norepinephrine reuptake inhibitors (SNRIs)
- medicines used to treat migraine headaches called triptans
- tricyclic antidepressants
- lithium
- fentanyl
- tramadol
- tryptophan
- buspirone
- St. John’s Wort

Know the medicines that you or your child take. Keep a list of your or your child’s medicines with you to show your healthcare provider and pharmacist when you or your child get a new medicine.

Do not start any new medicine during treatment with DEXEDRINE without talking to your healthcare provider first.

How should DEXEDRINE be taken?

- Take DEXEDRINE exactly as prescribed by your or your child’s healthcare provider.
- Your healthcare provider may change the dose if needed.
- DEXEDRINE is an extended-release capsule. It releases medicine into your body throughout the day.

If you or your child take too much DEXEDRINE, call your healthcare provider or Poison Help line at 1-800-222-1222 or go to the nearest hospital emergency room right away.

What are possible side effects of DEXEDRINE?

DEXEDRINE may cause serious side effects, including:

- See “What is the most important information I should know about DEXEDRINE?”
- Slowing of growth (height and weight) in children. Children should have their height and weight checked often during treatment with DEXEDRINE. Your healthcare provider may stop your child’s DEXEDRINE treatment if they are not growing or gaining weight as expected.
- Seizures. Your healthcare provider may stop treatment with DEXEDRINE if you or your child have a seizure.
- Circulation problems in fingers and toes (peripheral vasculopathy, including Raynaud’s phenomenon). Signs and symptoms may include:

- fingers or toes may feel numb, cool, painful
- fingers or toes may change color from pale, to blue, to red

Tell your healthcare provider if you or your child have numbness, pain, skin color change, or sensitivity to temperature in your fingers or toes.

Call your healthcare provider right away if you or your child have any signs of unexplained wounds appearing on fingers or toes during treatment with DEXEDRINE.

- New or worsening tics or worsening Tourette’s syndrome. Tell your healthcare provider if you or your child get any new or worsening tics or worsening Tourette’s syndrome during treatment with DEXEDRINE.
- Serotonin syndrome. This problem may happen when DEXEDRINE is taken with certain other medicines and may be life-threatening. Stop taking DEXEDRINE and call your healthcare provider or go to the nearest hospital emergency room right away if you or your child develop any of the following signs and symptoms of serotonin syndrome:

- agitation
- fast heartbeat
- flushing
- seizures
- coma
- sweating
- loss of coordination
- confusion
- dizziness
- tremors, stiff muscles, or muscle twitching
- seeing or hearing things that are not real (hallucination)
- changes in blood pressure
- high body temperature (hypothermia)
- onausea, vomiting, diarrhea

The most common side effects of DEXEDRINE include:

- fast heartbeat
- decreased appetite
- tremors
- headache
- trouble sleeping
- dizziness
- stomach upset
- weight loss
- dry mouth

These are not all of the possible side effects of DEXEDRINE. Call your doctor for medical advice about side effects. You may report side effects to FDA at 1-800-FDA-1088.

How should I store DEXEDRINE?

- Store DEXEDRINE at room temperature between 68° to 77°F (20° to 25°C).
- Store DEXEDRINE in a safe place, like a locked cabinet. Protect from light.
- Dispose of remaining, unused, or expired DEXEDRINE by a medicine take-back program at a U.S. Drug Enforcement Administration (DEA) authorized collection site. If no take-back program or DEA authorized collector is available, mix DEXEDRINE with an undesirable, nontoxic substance such as dirt, cat litter, or used coffee grounds to make it less appealing to children and pets. Place the mixture in a container such as a sealed plastic bag and throw away DEXEDRINE in the household trash. Visit www.fda.gov/drugdisposal for additional information on disposal of unused medicines.

Keep DEXEDRINE and all medicines out of the reach of children.

General information about the safe and effective use of DEXEDRINE.

Medicines are sometimes prescribed for purposes other than those listed in a Medication Guide. Do not use DEXEDRINE for a condition for which it was not prescribed. Do not give DEXEDRINE to other people, even if they have the same symptoms that you or your child have. It may harm them and it is against the law. You can ask your pharmacist or healthcare provider for information about DEXEDRINE that is written for healthcare professionals.

What are the ingredients in DEXEDRINE?

Active ingredient: dextroamphetamine sulfate

Inactive ingredients: cetyl alcohol, D&C Yellow No. 10, dibutyl sebacate, ethylcellulose, FD&C Blue No. 1, FD&C Red No. 40, FD&C Yellow No. 6, gelatin, hypromellose, polyethylene glycol, povidone, sodium lauryl sulfate, sugar spheres, and trace amounts of other inactive ingredients.

Manufactured by:

Catalent Pharma Solutions

Winchester, KY 40391

Distributed by:

Amneal Specialty, a division of

Amneal Pharmaceuticals LLC

Bridgewater, NJ 08807

For more information about DEXEDRINE, visit www.amneal.com or call 1-877-835-5472.

This Medication Guide has been approved by the U.S. Food and Drug Administration. Rev. 09-2025-01